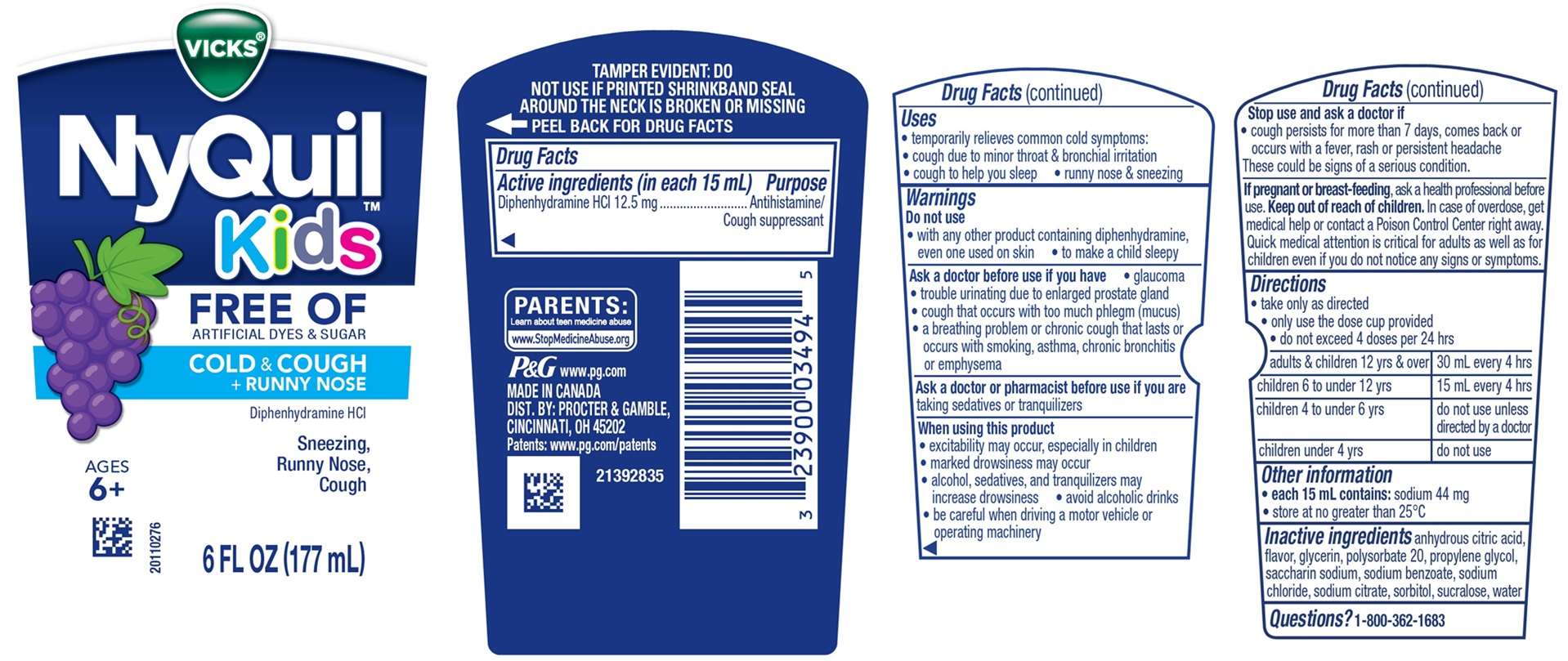 DRUG LABEL: VICKS NyQuil Kids

NDC: 84126-311 | Form: LIQUID
Manufacturer: The Procter & Gamble Manufacturing Company
Category: otc | Type: HUMAN OTC DRUG LABEL
Date: 20251201

ACTIVE INGREDIENTS: DIPHENHYDRAMINE HYDROCHLORIDE 12.5 mg/15 mL
INACTIVE INGREDIENTS: SODIUM BENZOATE; ANHYDROUS CITRIC ACID; WATER; SACCHARIN SODIUM; SODIUM CITRATE; GLYCERIN; SORBITOL; SUCRALOSE; POLYSORBATE 20; PROPYLENE GLYCOL; SODIUM CHLORIDE

Vicks®NyQuil™ Kids FREE OF ARTIFICIAL DYES & SUGAR COLD & COUGH + RUNNY NOSE, Liquid

Drug Facts

Active ingredient (in each 15 mL)

Diphenhydramine HCl 12.5 mg

Purpose

Antihistamine/Cough suppressant

Uses

- temporarily relieves common cold symptoms:
- cough due to minor throat & bronchial irritation
- cough to help you sleep
- runny nose & sneezing

Warnings

Do not use

- with any other product containing diphenhydramine, even one used on skin
- to make a child sleepy

Ask a doctor before use if you have

- glaucoma
- trouble urinating due to enlarged prostate gland
- cough that occurs with too much phlegm (mucus)
- a breathing problem or chronic cough that lasts or occurs with smoking, asthma, chronic bronchitis or emphysema

Ask a doctor or pharmacist before use if you are

taking sedatives or tranquilizers

When using this product

- excitability may occur, especially in children
- marked drowsiness may occur
- alcohol, sedatives, and tranquilizers may increase drowsiness
- avoid alcoholic drinks
- be careful when driving a motor vehicle or operating machinery

Stop use and ask a doctor if

- cough persists for more than 7 days, comes back or occurs with a fever, rash or persistent headache

These could be signs of a serious condition.

If pregnant or breast-feeding,

ask a health professional before use.

Keep out of reach of children.

OVERDOSAGE

In case of overdose, get medical help or contact a Poison Control Center right away. Quick medical attention is critical for adults as well as for children even if you do not notice any signs or symptoms.

Directions

- take only as directed
- only use the dose cup provided
- do not exceed 4 doses per 24 hrs

adults & children 12 yrs & over | 30 mL every 4 hrs
children 6 to under 12 yrs | 15 mL every 4 hrs
children 4 to under 6 yrs | do not use unless directed by a doctor
children under 4 yrs | do not use

Other information

- each 15 mL contains: sodium 44 mg
- store at no greater than 25°C

Inactive ingredients

anhydrous citric acid, flavor, glycerin, polysorbate 20, propylene glycol, saccharin sodium, sodium benzoate, sodium chloride, sodium citrate, sorbitol, sucralose, water

Questions or comments?

1-800-362-1683

TAMPER EVIDENT: DO NOT USE IF PRINTED SHRINKBAND SEAL AROUND THE NECK IS BROKEN OR MISSING

MADE IN CANADA

DIST. BY: PROCTER & GAMBLE

CINCINNATI, OH 45202

PRINCIPAL DISPLAY PANEL

VICKS®

NyQuil™

Kids

FREE OF

ARTIFICIAL DYES & SUGAR

COLD & COUGH + RUNNY NOSE

Diphenhydramine HCl

Sneezing, Runny Nose, Cough

AGES 6+

6 FL OZ (177 mL)